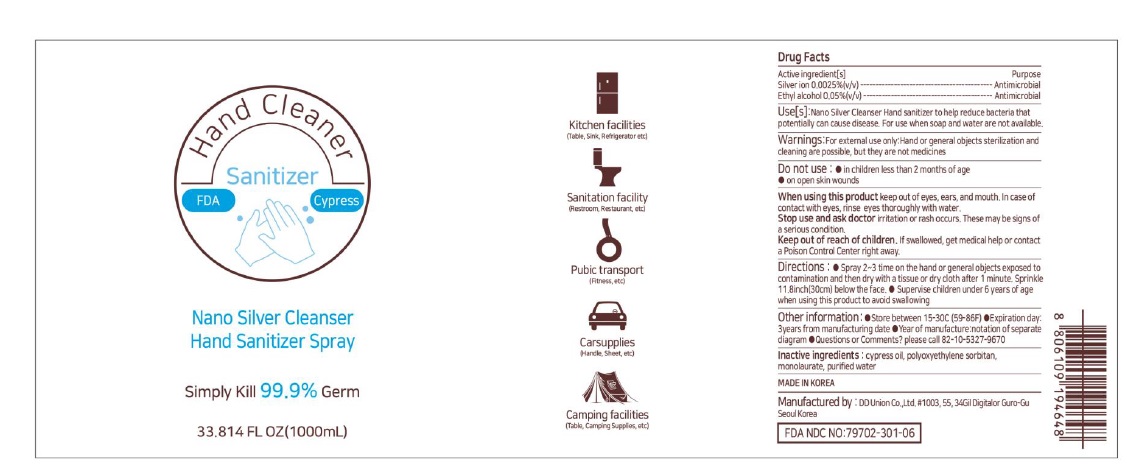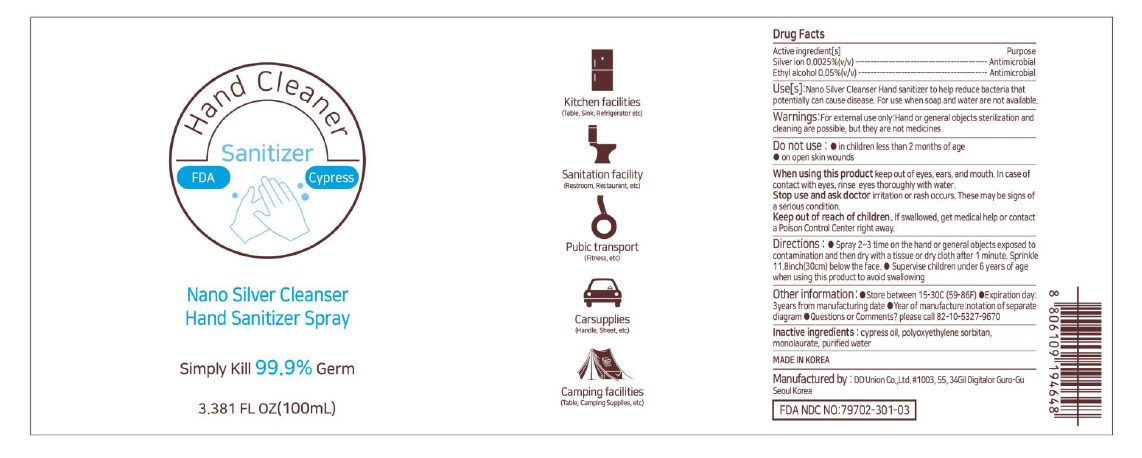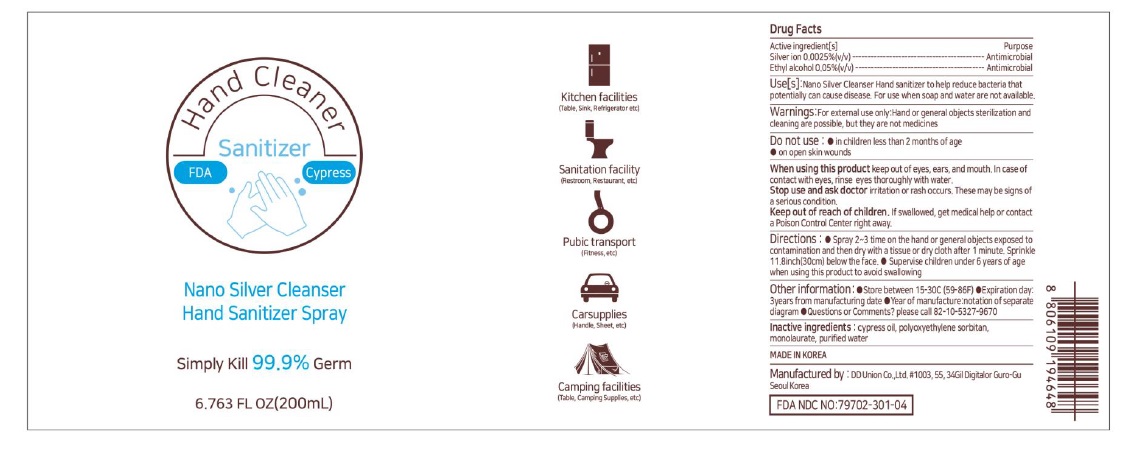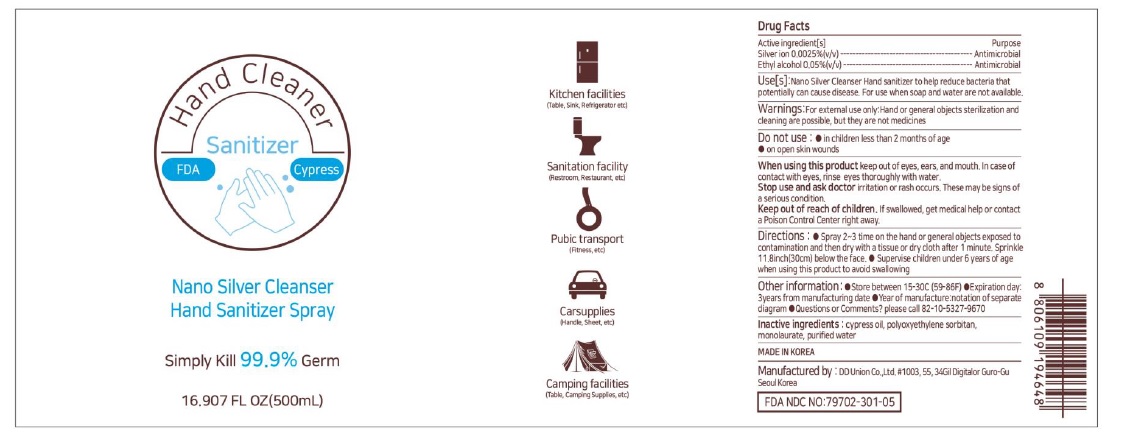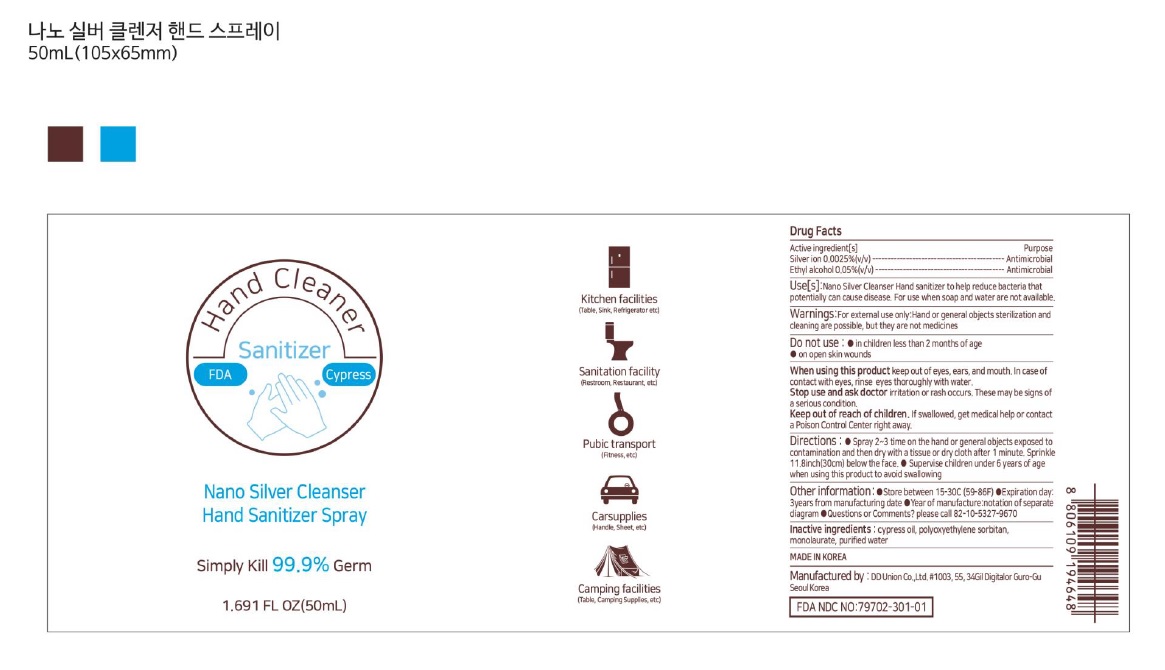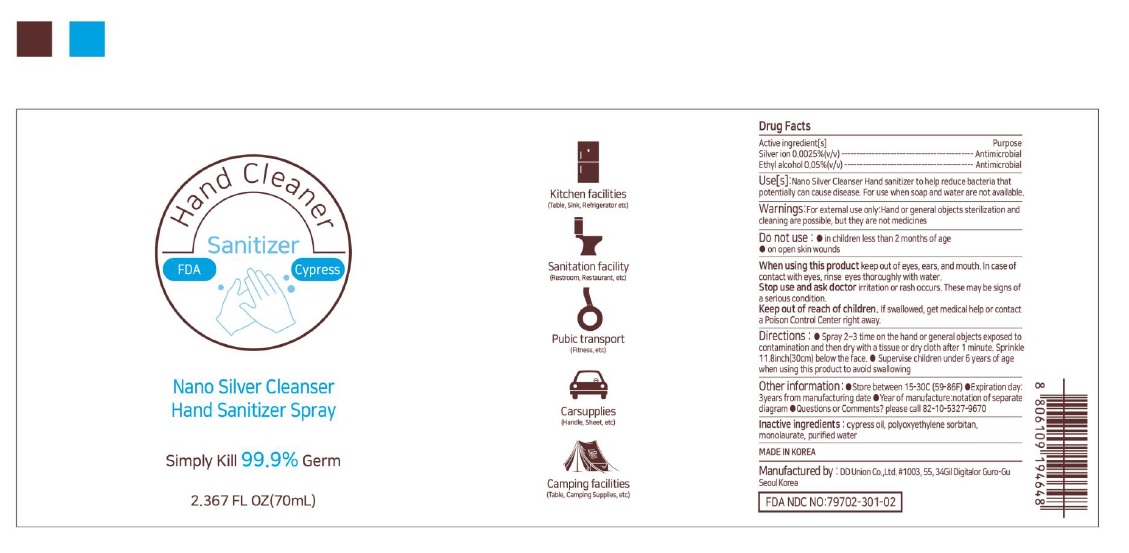 DRUG LABEL: Nano Silver Cleanser Hand Sanitizer
NDC: 79702-301 | Form: SPRAY
Manufacturer: DDUnion, Co.,Ltd
Category: otc | Type: HUMAN OTC DRUG LABEL
Date: 20201015

ACTIVE INGREDIENTS: SILVER CATION 0.0025 g/100 mL; ALCOHOL 0.05 mL/100 mL
INACTIVE INGREDIENTS: WATER; POLYSORBATE 20; CUPRESSUS SEMPERVIRENS LEAF OIL

Active ingredient

SILVER CATION,ALCOHOL

USE

Nano Silver Cleanser Hand sanitizer to help reduce bacteria that potentially can cause disease.

For use when soap and water are not available.

If you are new to the product, apply it on a small area and test

to see if there is anything wrong with your skin

WHEN USING

keep out of eyes, ears, and mouth. In case of contact with eyes, rinse eyes thoroughly with water.

Warnings

For external use only. Flammable. Keep away from heat or flame

Don't put it on your face

Hand sterilization and cleaning are possible, but they are

not medicines

Do not use

● in children less than 2 months of age

● on open skin wounds

Do not use in areas with abnormalities such as wound, eczema,

and dermatitis

Stop use and ask doctor irritation or rash occurs. These may be signs of a serious condition.

If you experience any of the following problems, do not use this product and contact your dermatologist, etc

In case of abnormalities such as red spots, swelling,

itching, irritation, etc. during use

PURPOSE

Antimicrobial

Keep out of reach of children

Direction

● Spray 2~3 time on the hand or general objects exposed to contamination and then dry with

a tissue or dry cloth after 1 minute. Sprinkle 30cm below the face.

● Supervise children under 6 years of age when using this product to avoid swallowing

Other information

●Store between 15-30C (59-86F)

●Avoid freezing and excessive heat above 40C (104F)

●Year of manufacture:notation of separate diagram

●Expiration day:3years from manufacturing date

●Questions or Comments? please call 82-10-5327-9670

Inactive ingredients

cypress oil, poiyoxyethylene sorbitan monolaurate, purified water

label

79702-301-01 50ML

79702-301-02 70ML

79702-301-03 100ML

79702-301-04 200ML

79702-301-05 500ML

79702-301-06 1000ML